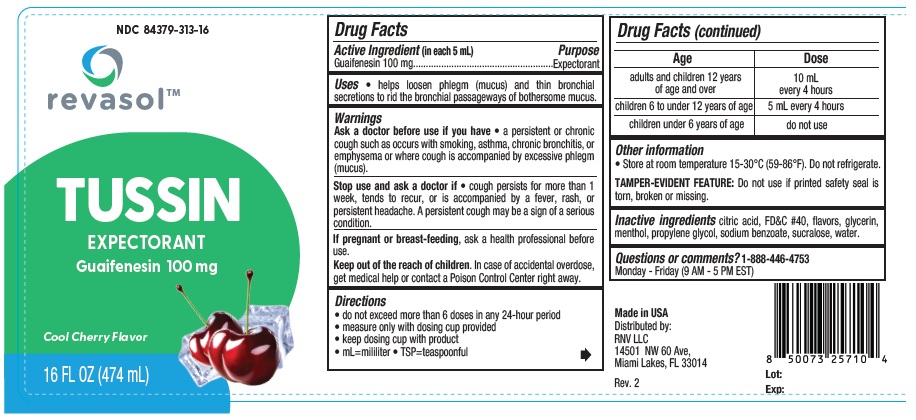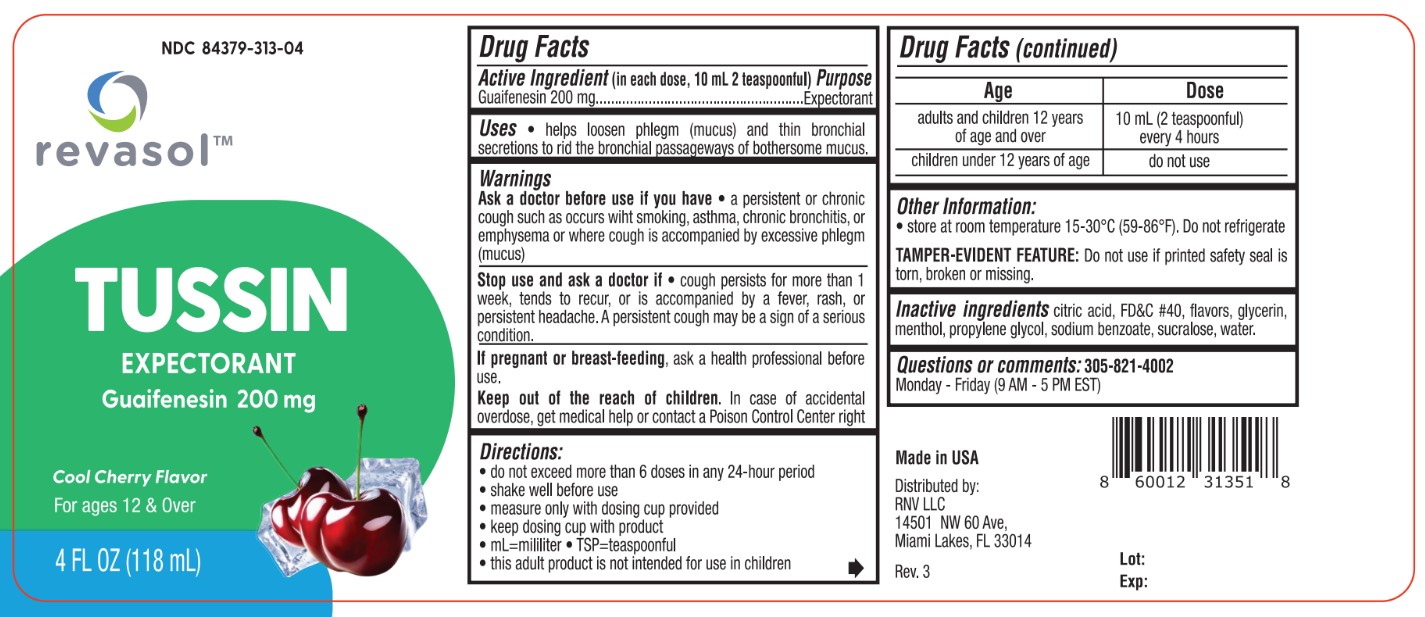 DRUG LABEL: Revasol Tussin
NDC: 84379-313 | Form: LIQUID
Manufacturer: Rnv LLC
Category: otc | Type: HUMAN OTC DRUG LABEL
Date: 20260223

ACTIVE INGREDIENTS: GUAIFENESIN 200 mg/10 mL
INACTIVE INGREDIENTS: WATER; ANHYDROUS CITRIC ACID; PROPYLENE GLYCOL; MENTHOL; GLYCERIN; SODIUM BENZOATE; FD&C RED NO. 40; SUCRALOSE

Revasol Tussin Cherry Flavor NDC 84379-313-04, 84379-313-16

ACTIVE INGREDIENT

Guafenesin 200 mg

PURPOSE

Expectorant

Uses

helps loosen phlegm (mucus) and thin bronchial
secretions to rid the bronchial passageways of bothersome mucus.

Warning

Ask a doctor before use if you have • a persistent or chronic
cough such as occurs wiht smoking, asthma, chronic bronchitis, or
emphysema or where cough is accompanied by excessive phlegm
(mucus)

Stop use and ask a doctor if • cough persists for more than 1
week, tends to recur, or is accompanied by a fever, rash, or
persistent headache. A persistent cough may be a sign of a serious
condition.

PREGNANCY OR BREAST FEEDING

If pregnant or breast-feeding, ask a health professional before
use.

KEEP OUT OF REACH OF CHILDREN

Keep out of the reach of children. In case of accidental overdose,
get medical help or contact a Poison Control Center right away.

Directions:

- do not exceed more than 6 doses in any 24-hour period
- shake well before use
- measure only with dosing cup provided
- keep dosing cup with product
- mL=mililiter • TSP=teaspoonful
- this adult product is not intended for use in children

Age | Dose
adults and children 12 years of age and over | 10 mL (2 teaspoonful) every 4 hours
children under 12 years of age | do not use

INACTIVE INGREDIENT

Inactive ingredients citric acid, FD&C #40, flavors, glycerin,
menthol, propylene glycol, sodium benzoate, sucralose, water.

Questions or comments? 1-888-446-4753
Monday - Friday (9 AM - 5 PM EST)

Other Information:

- store at room temperature 15-30°C (59-86ºF). Do not refrigerate

TAMPER-EVIDENT FEATURE: Do not use if printed safety seal is torn, broken or missing.

Made in USA

Distributed by:

RNV LLC

14501 NW 60 Ave,

Miami Lakes, FL 33014